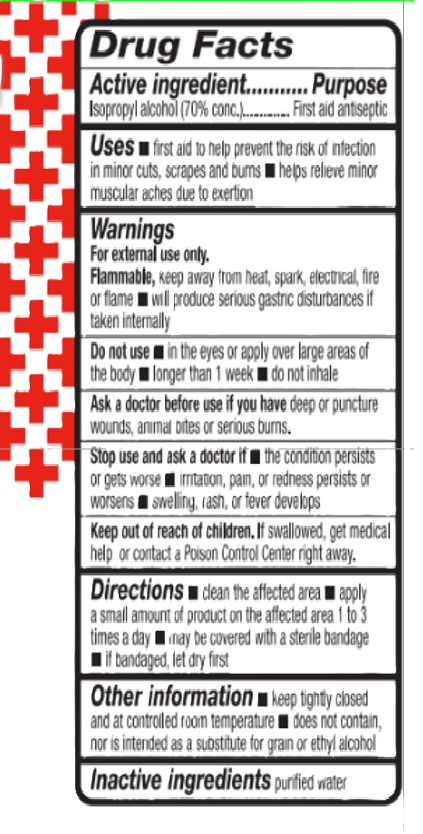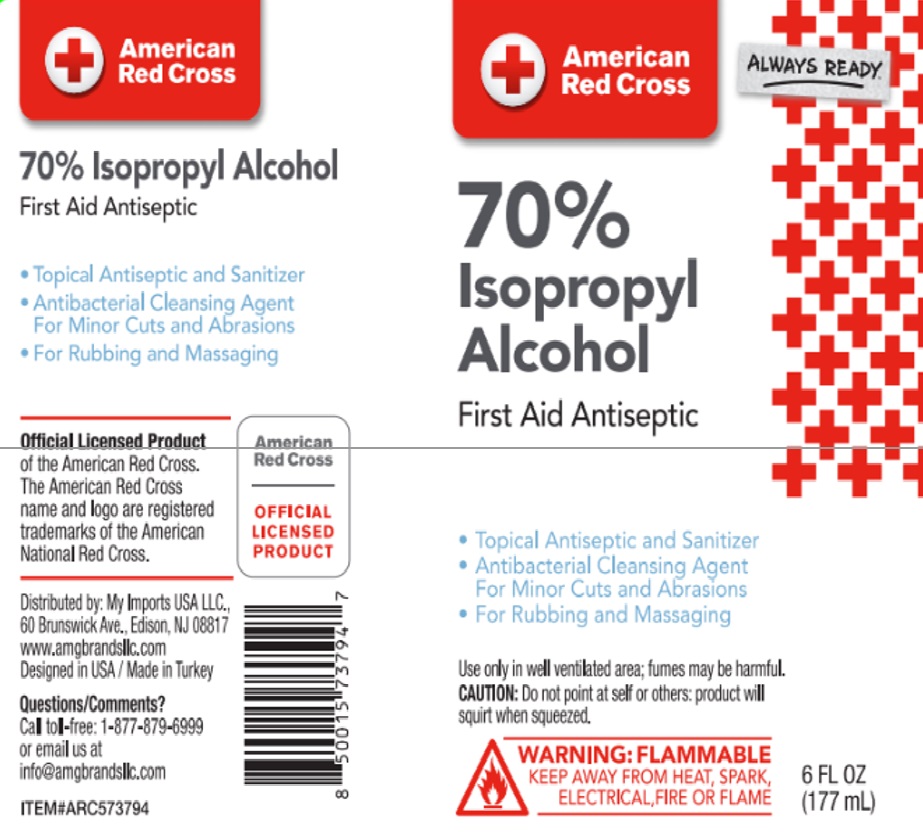 DRUG LABEL: American Red Cross Isopropyl Alcohol 70% 6oz
NDC: 76567-3794 | Form: SPRAY
Manufacturer: TSM BRANDS LLC
Category: otc | Type: HUMAN OTC DRUG LABEL
Date: 20241230

ACTIVE INGREDIENTS: ISOPROPYL ALCOHOL 124 mL/177 mL
INACTIVE INGREDIENTS: AQUA 53 mL/177 mL

AMERICAN RED CROSS 70% IPA 6OZ

ACTIVE INGREDIENT

Active ingredient ....... Purpose

Isopropyl alcohol (70% conc)........ First aid antiseptic

USES

first aid to help prevent the risk of infection in minor cuts, scrapes and burns.

helps relieve minor muscular aches due to exertion

Ask a doctor before use if you have deep or puncture wounds, animal bites or serious burns.

STOP USE

Stop use and ask a doctor if the condition persists or gets worse

irritation, pain or redness persists or worsens

swelling, rash or fever develops

DO NOT USE

in the eyes or apply over large areas of the body

longer than 1 week

do not inhale

Keep out of reach of children. If swallowed, get medical help or contact a Poison Control Center right away.

INACTIVE INGREDIENTS

Inactive ingredients: purified water

WARNINGS

For external use only.

Flammable, keep away from heat, spark, ekectrical, fire or flame. will produce serious gastric disturbances if taken internally.

DIRECTIONS

clean the affected area

apply a small amount of product on the affected area 1 to 3 times a day

may be covered with a sterile bandage

if bandaged, let it dry first

OTHER INFORMATION

leep tightly closed and at controlled room temperature

does not contain, nor is intended as a substitute for grain or ethyl alcohol

DIRECTIONS

clean the affected area

apply a small amount of product on the affected area 1 to 3 times a day

may be covered with a sterile bandage

if bandaged, let it dry first